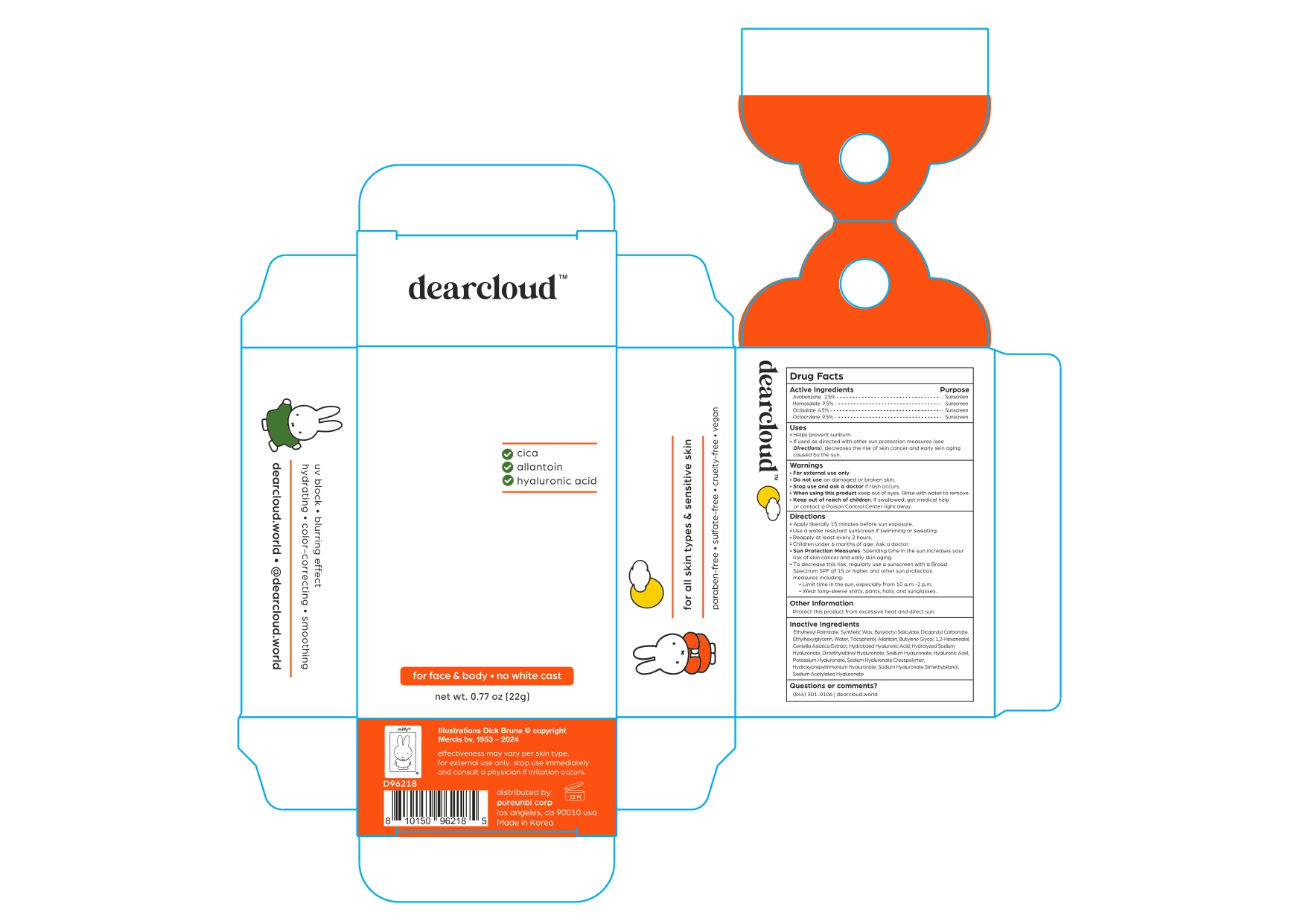 DRUG LABEL: Miffy Sunny Defense SPF Stick
NDC: 84326-424 | Form: STICK
Manufacturer: RBGROUP Co., Ltd
Category: otc | Type: HUMAN OTC DRUG LABEL
Date: 20251021

ACTIVE INGREDIENTS: AVOBENZONE 0.55 g/22 g; HOMOSALATE 2.09 g/22 g; OCTOCRYLENE 2.09 g/22 g; OCTISALATE 0.99 g/22 g
INACTIVE INGREDIENTS: 1,2-HEXANEDIOL; WATER; BUTYLENE GLYCOL; HYALURONATE SODIUM; ETHYLHEXYL PALMITATE; ETHYLHEXYLGLYCERIN; DICAPRYLYL CARBONATE; BUTYLOCTYL SALICYLATE; TOCOPHEROL; DIMETHYLSILANOL HYALURONATE; ALLANTOIN; CENTELLA ASIATICA TRITERPENOIDS; SODIUM ACETYLATED HYALURONATE

84326-424 Miffy Sunny Defense SPF Stick

ACTIVE INGREDIENT

Avobenzone 2.5%

Homosalate 9.5%

Octisalate 4.5%

Octocrylene 9.5%

PURPOSE

Sunscreen

INDICATIONS AND USAGE

● Helps prevent sunburn.

● If used as directed with other sun protection measures (See Directions), decreases the risk of skin cancer and early skin aging caused by the sun.

WARNINGS

For external use only

DO NOT USE

● on damaed skin or broken skin

STOP USE

and ask a doctor if rash occurs.

WHEN USING

● Keep out of eyes. Rinse with water to remove.

KEEP OUT OF REACH OF CHILDREN

If swallowed, get medical help or contact a Poison Control Center right away.

OTHER SAFETY INFORMATION

● Protect this product from excessive heat and direct sun.

Directions

● Apply liberally 15 minutes before sun exposure.

● Use a water resistant sunscreen if swimming or swating.

● Reapply at least every 2 hours.

● Children under 6 months of age: Ask a doctor.

● Sun Protection Measures. Spending time in the sun increases your risk of skin cancer and early skin aging. To decrease this risk, regularly use a sunscreen other sun protection measures including: ● Limit time in the sun, especially from 10 a.m. - 2 p.m. ● Wear long-sleeve shirts, pants, hats, and sunglasses.

INACTIVE INGREDIENT

Ethylhexyl Palmitate, Synthetic Wax, Butyloctyl Salicylate, Dicaprylyl Carbonate, Ethylhexylglycerin, Water, Tocopherol, Allantoin, Butylene Glycol, 1,2-Hexanediol, Centella Asiatica Extract, Hydrolyzed Hyaluronic Acid, Hydrolyzed Sodium Hyaluronate, Dimethylsilanol Hyaluronate, Sodium Hyaluronate, Hyaluronic Acid, Potassium Hyaluronate, Sodium Hyaluronate Crosspolymer, Hydroxypropyltrimonium Hyaluronate, Sodium Hyaluronate Dimethylsilanol, Sodium Acetylated Hyaluronate